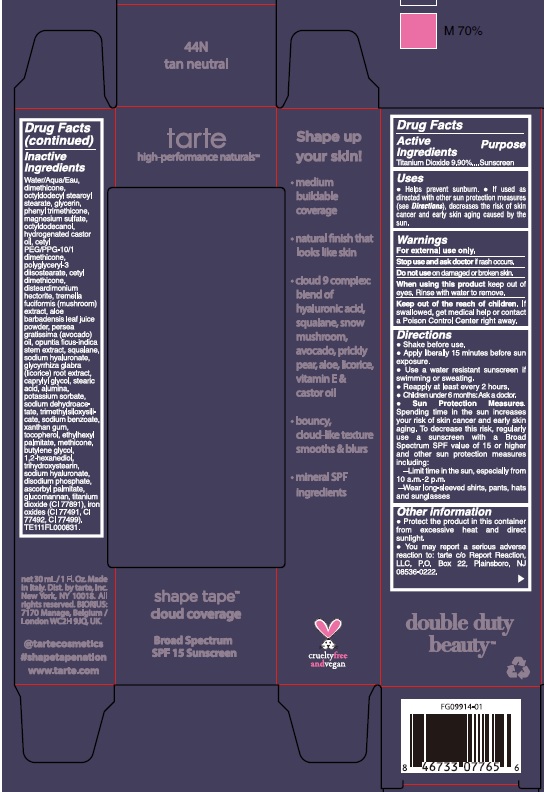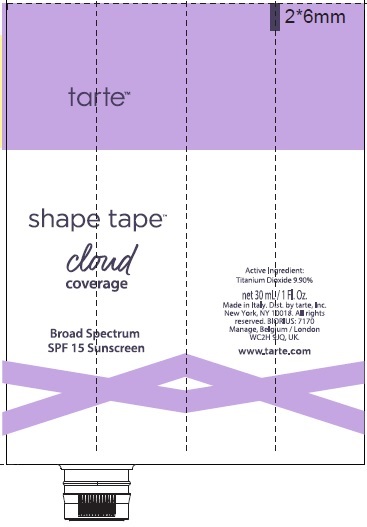 DRUG LABEL: Titanium Dioxide
NDC: 66888-343 | Form: CREAM
Manufacturer: Tecnocosmesi S.p.A
Category: otc | Type: HUMAN OTC DRUG LABEL
Date: 20250203

ACTIVE INGREDIENTS: TITANIUM DIOXIDE 99 mg/1 mL
INACTIVE INGREDIENTS: POLYGLYCERYL-3 DIISOSTEARATE; WATER; AVOCADO OIL; OPUNTIA FICUS-INDICA STEM; GLYCYRRHIZA GLABRA; POTASSIUM SORBATE; ETHYLHEXYL PALMITATE; KONJAC MANNAN; TOCOPHEROL; DIMETHICONE; OCTYLDODECANOL; DISTEARDIMONIUM HECTORITE; TREMELLA FUCIFORMIS WHOLE; HYDROGENATED CASTOR OIL; TRIHYDROXYSTEARIN; ASCORBYL PALMITATE; ALUMINUM OXIDE; DIMETHICONOL/TRIMETHYLSILOXYSILICATE CROSSPOLYMER (35/65 W/W; 10000000 PA.S); 1,2-HEXANEDIOL; PEG-9 DIGLYCIDYL ETHER/SODIUM HYALURONATE CROSSPOLYMER; CETYL DIMETHICONE/BIS-VINYLDIMETHICONE CROSSPOLYMER; MAGNESIUM SULFATE, UNSPECIFIED; CETYL PEG/PPG-10/1 DIMETHICONE (HLB 2); FERRIC OXIDE RED; SODIUM BENZOATE; BUTYLENE GLYCOL; SODIUM DEHYDROACETATE; SQUALANE; CAPRYLYL GLYCOL; STEARIC ACID; XANTHAN GUM; FERRIC OXIDE YELLOW; FERROSOFERRIC OXIDE; OCTYLDODECYL STEAROYL STEARATE; GLYCERIN; PHENYL TRIMETHICONE; ALOE VERA LEAF; METHICONE (20 CST); SODIUM PHOSPHATE, DIBASIC, ANHYDROUS

Double Duty Beauty | Shape Tape | Cloud Coverage Broad Spectrum SPF 15 Sunscreen | 44N tan neutral

Active Ingredients

Titanium Dioxide 9.90%

Purpose

Suncreen

Uses

- Helps prevent sunburn
- If used as directed with other sun protection measures (see Directions), decreases the risk of skin cancer and early skin aging caused by the sun.

Warnings

For external use only.

Stop use and ask doctor

if rash occurs.

Do not use

on damaged or broken skin.

When using this product

keep out of eyes. Rinse with water to remove.

Keep out of the reach of children.

If swallowed, get medical help or contact a Poison Control Center right away.

Directions

Shake before use.

Apply liberally 15 minutes before sun exposure

Use a water resistant sunscreen if swimming or sweating.

Reapply at least every 2 hours.

Children under 6 months: Ask a doctor.

Sun Protection Measures. Spending time in the sun increases your risk of skin cancer and early skin aging. To decrease this risk, regularly use a sunscreen with a Broad Spectrum SPF value of 15 or higher and other sun protection measures including:

- Limit time in the sun, especially from 10 a.m.-2 p.m.

- Wear long-sleeved shirts, pants, hats and sunglasses

Other information

Protect the product in this container from excessive heat and direct sunlight.

You may report a serious adverse reaction to tarte c/o Report Reaction, LLC, P.O. Box 22, Plainsboro, NJ 08536-0222.

Inactive Ingredients

Water/Aqua/Eau, dimethicone, octyldodecyl stearoyl stearate, glycerin, phenyl trimethicone, magnesium sulfate, octyldodecanol, hydrogenated castor oil, cetyl PEG/PPG-10/1 dimethicone, polyglyceryl-3 diisostearate, cetyl dimethicone, disteardimonium hectorite, tremella fuciformis (mushroom) extract, aloe barbadensis leaf juice powder, persea gratissima (avocado) oil, opuntia ficus-indica stem extract, squalane, sodium hyaluronate, glycyrrhiza glabra (licorice) root extract, caprylyl glycol, stearic acid, alumina, potassium sorbate, sodium dehydroacetate, trimethylsiloxysilicate, sodium benzoate, xanthan gum, tocopherol, ethylhexyl palmitate, methicone, butylene glycol, 1,2-hexanediol, trihydroxystearin, sodium hyaluronate, disodium phosphate, ascorbyl palmitate, glucomannan, titanium dioxide (CI 77891), iron oxides (CI 77491, CI 77492, CI 77499), TE111FL000831.

Principal Display Panel

tarte

high performance naturals

shape tape

cloud coverage

Broad Spectrum

SPF 15 Sunscreen